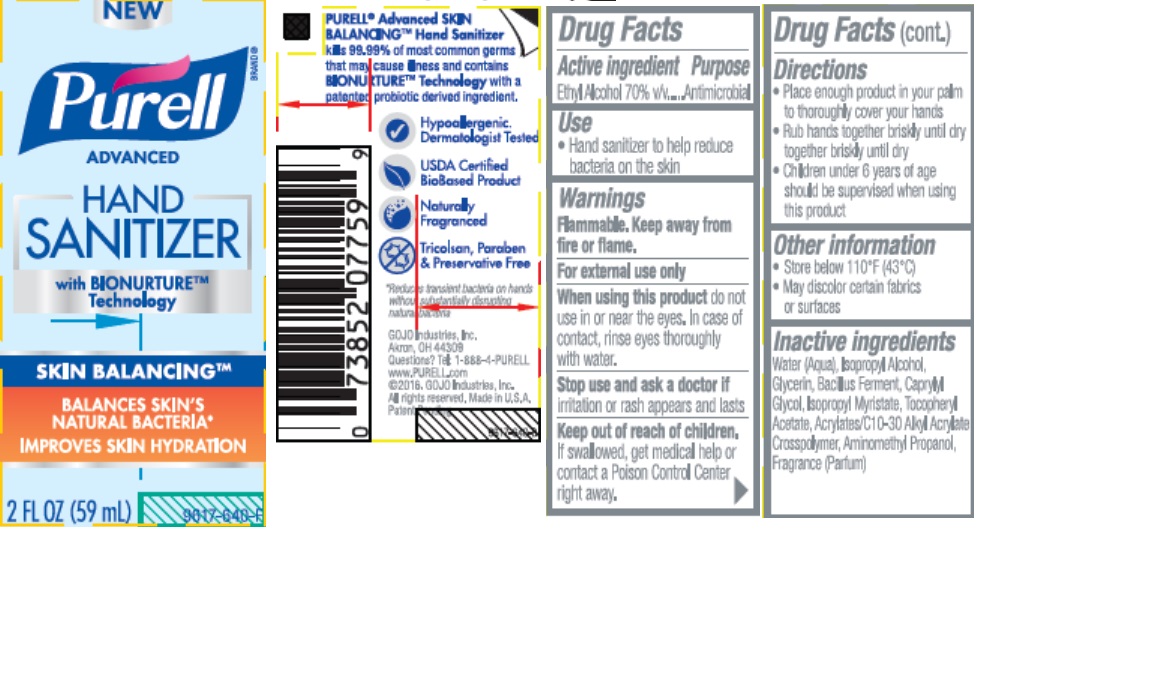 DRUG LABEL: PURELL Advanced Skin Balancing Hand Sanitizer
NDC: 21749-480 | Form: GEL
Manufacturer: GOJO Industries, Inc.
Category: otc | Type: HUMAN OTC DRUG LABEL
Date: 20161209

ACTIVE INGREDIENTS: ALCOHOL 0.7 mL/1 mL
INACTIVE INGREDIENTS: WATER; ISOPROPYL ALCOHOL; GLYCERIN; CAPRYLYL GLYCOL; ISOPROPYL MYRISTATE; .ALPHA.-TOCOPHEROL ACETATE; CARBOMER INTERPOLYMER TYPE A (ALLYL SUCROSE CROSSLINKED); AMINOMETHYLPROPANOL

PURELL Advanced Skin Balancing Hand Sanitizer

Active Ingredient

Ethyl Alcohol 70%

Purpose

Antimicrobial

Use

Hand Sanitizer to help reduce bacteria on skin

Warnings

Flammable. Keep away from fire or flame.

For external use only

When using this product do not use in or near the eyes. In case of contact, rinse eyes thoroughly with water.

Stop use and ask a doctor if irritation or rash appears and lasts

Keep out of reach of children. If swallowed, get medical help or contact a Poison Control Center right away.

Directions

- Place enough product in your palm to thoroughly cover your hands
- Rub hands together briskly until dry
- Children under 6 years of age should be supervised when using this product.

Other information

• Store below 110°F (43°C) • May discolor certain fabrics or surfaces

Inactive ingredients

Water (Aqua), Isopropyl Alcohol, Glycerin, Bacillus Ferment, Caprylyl Glycol, Isopropyl Myristate, Tocopheryl Acetate, Acrylates/C10-30 Alkyl Acrylate Crosspolymer, Aminomethyl Propanol, Fragrance (Parfum)